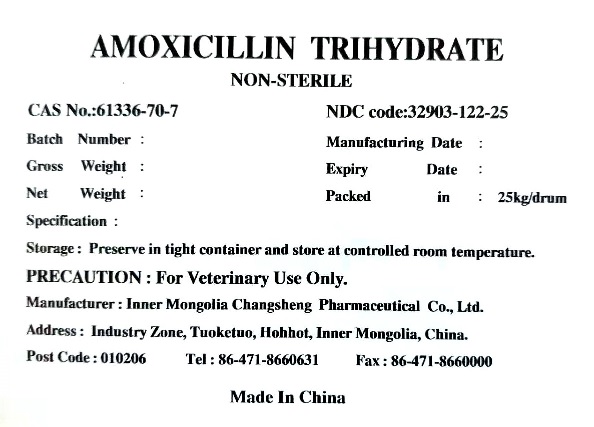 DRUG LABEL: Amoxicillin Trihydrate
NDC: 32903-122 | Form: POWDER
Manufacturer: Inner Mongolia Changsheng Pharmaceutical Co., Ltd.
Category: other | Type: BULK INGREDIENT - ANIMAL DRUG
Date: 20251230

ACTIVE INGREDIENTS: AMOXICILLIN 1 kg/1 kg

PACKAGE LABEL

AMOXICILLIN TRIHYDRATE

NON-STERILE

CAS NO.:61336-70-7 NDC code:32903-122-25

Batch Number : Manufacturing Date :

Gross Weight : Expiry Date :

Net Weight : Packed in : 25kg/drum

Specification :

Storage : Preserve in tight container and store at controlled room temperature.

PRECAUTION : For Veterinary Use Only.

Manufacturer : Inner Mongolia Changsheng Pharmaceutical Co., Ltd.

Address : Industry Zone, Tuoketuo, Hohhot, Inner Mongolia, China.

Post Code : 010206 Tel : 86-471-8660631 Fax : 86-471-8660000

Made in China